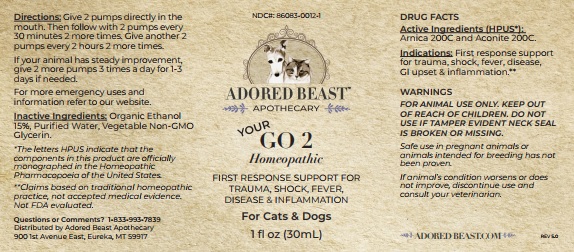 DRUG LABEL: YOUR GO 2
NDC: 86083-0012 | Form: LIQUID
Manufacturer: The Adored Beast Apothecary, Ltd
Category: homeopathic | Type: OTC ANIMAL DRUG LABEL
Date: 20251027

ACTIVE INGREDIENTS: ARNICA MONTANA WHOLE 200 [hp_C]/30 mL; ACONITUM NAPELLUS ROOT 200 [hp_C]/30 mL
INACTIVE INGREDIENTS: ALCOHOL; WATER; GLYCERIN

YOUR GO 2

DRUG FACTS
Active Ingredients (HPUS*):
Arnica 200C and Aconite 200C

*The letters HPUS indicate that the components in this product are officially monographed in the Homeopathic Pharmacopoeia of the United States.
**Claims based on traditional homeopathic practice, not accepted medical evidence. Not FDA evaluated.

INDICATIONS AND USAGE

Indications: First response support for trauma, shock, fever, disease, GI upset & inflammation.**

WARNINGS

FOR ANIMAL USE ONLY. KEEP OUT OF REACH OF CHILDREN. DO NOT USE IF TAMPER EVIDENT NECK SEAL
IS BROKEN OR MISSING.

Safe use in pregnant animals or animals intended for breeding has not been proven.

If animal’s condition worsens or does not improve, discontinue use and consult your veterinarian.

KEEP OUT OF REACH OF CHILDREN

DOSAGE AND ADMINISTRATION

Directions:Give 2 pumps directly in the mouth. Then follow with 2 pumps every 30 minutes 2 more times. Give another 2 pumps every 2 hours 2 more times. If your animal has steady improvement, give 2 more pumps 3 times a day for 1-3 days if needed. For more emergency uses and
information refer to our website.

INACTIVE INGREDIENT

Inactive Ingredients: Organic Ethanol 15%, Purified Water, Vegetable Non-GMO Glycerin.

Questions or Comments? 1-833-993-7839

Distributed by Adored Beast Apothecary

900 1st Avenue East, Eureka, MT 59917

PACKAGE LABEL

NDC#: 86083-0012-1

ADORED BEAST

APOTHECARY

YOUR GO 2

Homeopathic

FIRST RESPONSE SUPPORT FOR
TRAUMA, SHOCK, FEVER,
DISEASE & INFLAMMATION

For Cats & Dogs

1 fl oz (30mL)

PURPOSE

First response support for trauma, shock, fever, disease, GI upset & inflammation.